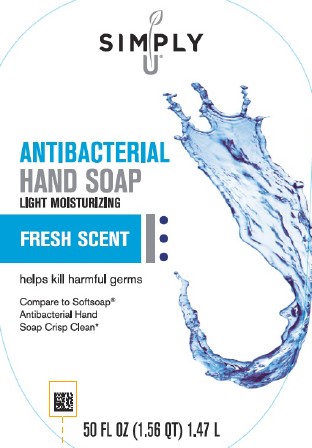 DRUG LABEL: Moisturizing Antibacterial
NDC: 11344-279 | Form: SOAP
Manufacturer: Consumer Product Partners, LLC
Category: otc | Type: HUMAN OTC DRUG LABEL
Date: 20250211

ACTIVE INGREDIENTS: BENZALKONIUM CHLORIDE 1.3 mg/1 mL
INACTIVE INGREDIENTS: WATER; LAURAMINE OXIDE; COCAMIDOPROPYL BETAINE; LAURAMIDOPROPYLAMINE OXIDE; SODIUM CHLORIDE; MYRISTAMIDOPROPYLAMINE OXIDE; GLYCERIN; DISTEARETH-75 ISOPHORONE DIISOCYANATE; PEG-150 DISTEARATE; CITRIC ACID MONOHYDRATE; EDETATE SODIUM; SULISOBENZONE; SODIUM BENZOATE; D&C RED NO. 33; FD&C RED NO. 40; FD&C YELLOW NO. 5

Simply U 279.003/279AE
Light Moisturizing Antibacterial Hand Soap

Claims

ANTIBACTERIAL HAND SOAP

LIGHT MOISTURIZING

Active ingredient

Benzalkonium chloride 0.13%

Purpose

Antibacterial

Use

for handwashing to decrease bacteria on the skin

Warnings

For external use only: hands only

When using this product

- avoid contact with eyes. If contact occurs, rinse eyes thoroughly with water

Stop use and ask a doctor if

- irritation or redness develops
- condition persists for more than 72 hours

Keep out of reach of children

If swallowed, get medical help or contact a Poison Control Center right away.

Directions

- wet hands
- apply palmful to hands
- scrub thoroughly
- rinse thoroughly

Inactive ingredients

water, lauramine oxide, cocamidopropyl betaine, lauramidopropylamine oxide, sodium chloride, myristamidopropylamine oxide, glycerin, fragrance, disteareth-75 IPDI, PEG-150 distearate, citric acid, tetrasodium EDTA, benzophenone-4, sodium benzoate, red 33, red 40, yellow 5

Questions?

1-888-593-0593

Disclaimer

*This product is not manufactured or distributed by Colgate-Palmolive Company, distributor of Softsoap® Antibacterial Hand Soap Crisp Clean.

Adverse reaction

Distributed By:

Consumer Product Partners, LLC

St. Louis, MO 63114

Principal display panel

Simply U®

ANTIBACTERIAL HAND SOAP

LIGHT MOISTURIZING

FRESH SCENT

helps kill harmful germs

Compare to Softsoap® Antibacterial Hand Soap Crisp Clean*

50 FL OZ (1.56 QT) 1.47 L